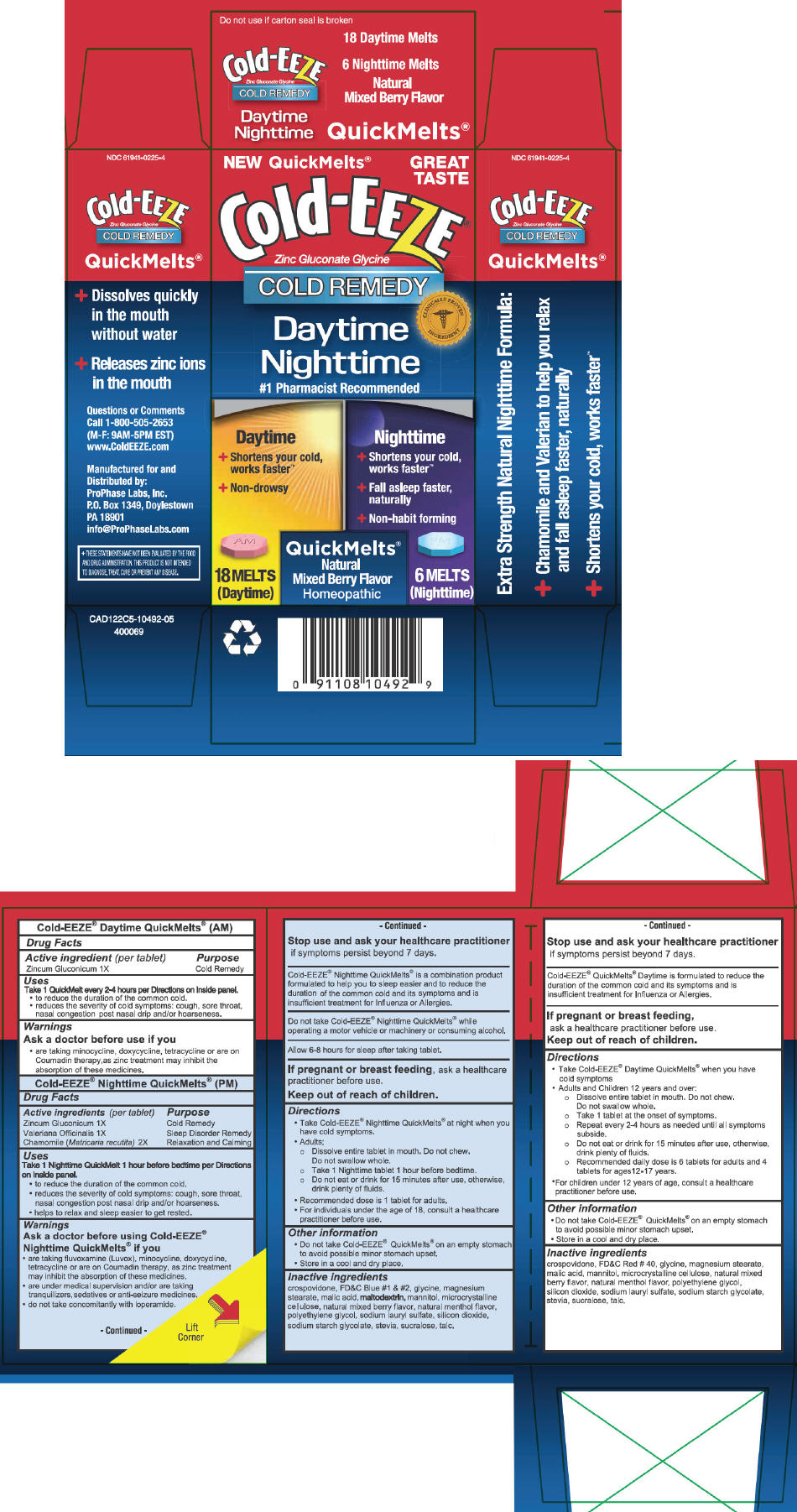 DRUG LABEL: Cold-EEZE 
NDC: 61941-0225 | Form: KIT | Route: ORAL
Manufacturer: ProPhase Labs, Inc.
Category: homeopathic | Type: HUMAN OTC DRUG LABEL
Date: 20141125

ACTIVE INGREDIENTS: Zinc Gluconate 1 [hp_X]/1 1; Zinc Gluconate 1 [hp_X]/1 1; VALERIAN 1 [hp_X]/1 1; Chamomile 2 [hp_X]/1 1
INACTIVE INGREDIENTS: Glycine; MALIC ACID; Crospovidone; FD&C RED NO. 40; MAGNESIUM STEARATE; MANNITOL; CELLULOSE, MICROCRYSTALLINE; POLYETHYLENE GLYCOLS; SODIUM LAURYL SULFATE; SILICON DIOXIDE; SODIUM STARCH GLYCOLATE TYPE A POTATO; STEVIA REBAUDIUNA LEAF; SUCRALOSE; TALC; Glycine; MALIC ACID; Crospovidone; FD&C BLUE NO. 1; FD&C BLUE NO. 2; MAGNESIUM STEARATE; MALTODEXTRIN; MANNITOL; CELLULOSE, MICROCRYSTALLINE; POLYETHYLENE GLYCOLS; SODIUM LAURYL SULFATE; SILICON DIOXIDE; SODIUM STARCH GLYCOLATE TYPE A POTATO; STEVIA REBAUDIUNA LEAF; SUCRALOSE; TALC

Cold-EEZE®
Daytime/Nighttime QuickMelts®

Cold-EEZE® Daytime QuickMelts® (AM)

Drug Facts

Active ingredient (per tablet)

Zincum Gluconicum 1X

Purpose

Cold Remedy

Uses

Take 1 QuickMelt every 2-4 hours per Directions on inside panel.

- to reduce the duration of the common cold.
- reduces the severity of cold symptoms: cough, sore throat, nasal congestion post nasal drip and/or hoarseness.

Warnings

Ask a doctor before use if you

- are taking minocycline, doxycycline, tetracycline or are on Coumadin therapy, as zinc treatment may inhibit the absorption of these medicines.

Stop use and ask your healthcare practitioner if symptoms persist beyond 7 days.

WHEN USING

Cold-EEZE® QuickMelts® Daytime is formulated to reduce the duration of the common cold and its symptoms and is insufficient treatment for Influenza or Allergies.

PREGNANCY OR BREAST FEEDING

If pregnant or breast feeding, ask a healthcare practitioner before use.

Keep out of reach of children.

Directions

- Take Cold-EEZE® Daytime QuickMelts® when you have cold symptoms
- Adults and Children 12 years and over:
  - Dissolve entire tablet in mouth. Do not chew.
    Do not swallow whole.
  - Take 1 tablet at the onset of symptoms.
  - Repeat every 2-4 hours as needed until all symptoms subside.
  - Do not eat or drink for 15 minutes after use, otherwise, drink plenty of fluids.
  - Recommended daily dose is 6 tablets for adults and 4 tablets for ages 12-17 years.
- For children under 12 years of age, consult a healthcare practitioner before use.

Other information

- Do not take Cold-EEZE® QuickMelts® on an empty stomach to avoid possible minor stomach upset.
- Store in a cool and dry place.

Inactive ingredients

crospovidone, FD&C Red # 40, glycine, magnesium stearate, malic acid, mannitol, microcrystalline cellulose, natural mixed berry flavor, natural menthol flavor, polyethylene glycol, silicon dioxide, sodium lauryl sulfate, sodium starch glycolate, stevia, sucralose, talc.

Cold-EEZE® Nighttime QuickMelts® (PM)

Drug Facts

ACTIVE INGREDIENT

Active ingredients (per tablet) | Purpose
Zincum Gluconicum 1X | Cold Remedy
Valeriana Officinalis 1X | Sleep Disorder Remedy
Chamomile (Matricaria recutita) 2X | Relaxation and Calming

Uses

Take 1 Nighttime QuickMelt 1 hour before bedtime per Directions on inside panel.

- to reduce the duration of the common cold.
- reduces the severity of cold symptoms: cough, sore throat, nasal congestion post nasal drip and/or hoarseness.
- helps to relax and sleep easier to get rested.

Warnings

Ask a doctor before using Cold-EEZE®

Nighttime QuickMelts® if you

- are taking fluvoxamine (Luvox), minocycline, doxycycline, tetracycline or are on Coumadin therapy, as zinc treatment may inhibit the absorption of these medicines.
- are under medical supervision and/or are taking tranquilizers, sedatives or anti-seizure medicines.
- do not take concomitantly with loperamide.

Stop use and ask your healthcare practitioner if symptoms persist beyond 7 days.

WHEN USING

Cold-EEZE® Nighttime QuickMelts® is a combination product formulated to help you to sleep easier and to reduce the duration of the common cold and its symptoms and is insufficient treatment for Influenza or Allergies.

DO NOT USE

Do not take Cold-EEZE® Nighttime QuickMelts® while operating a motor vehicle or machinery or consuming alcohol.

Allow 6-8 hours for sleep after taking tablet.

PREGNANCY OR BREAST FEEDING

If pregnant or breast feeding, ask a healthcare practitioner before use.

Keep out of reach of children.

Directions

- Take Cold-EEZE® Nighttime QuickMelts® at night when you have cold symptoms.
- Adults;
  - Dissolve entire tablet in mouth. Do not chew.
    Do not swallow whole.
  - Take 1 Nighttime tablet 1 hour before bedtime.
  - Do not eat or drink for 15 minutes after use, otherwise, drink plenty of fluids.
- Recommended dose is 1 tablet for adults.
- For individuals under the age of 18, consult a healthcare practitioner before use.

Other information

- Do not take Cold-EEZE® QuickMelts® on an empty stomach to avoid possible minor stomach upset.
- Store in a cool and dry place.

Inactive ingredients

crospovidone, FD&C Blue #1 & #2, glycine, magnesium stearate, malic acid, maltodextrin, mannitol, microcrystalline cellulose, natural mixed berry flavor, natural menthol flavor, polyethylene glycol, sodium lauryl sulfate, silicon dioxide, sodium starch glycolate, stevia, sucralose, talc.

Questions or Comments

Call 1-800-505-2653 (M-F: 9AM-5PM EST)

Manufactured for and
Distributed by:
ProPhase Labs, Inc.
P.O. Box 1349, Doylestown
PA 18901

PRINCIPAL DISPLAY PANEL - Kit Carton

NEW QuickMelts®

GREAT
TASTE

Cold-EEZE®
Zinc Gluconate Glycine
COLD REMEDY

CLINICALLY PROVEN
INGREDIENT

Daytime
Nighttime
#1 Pharmacist Recommended

Daytime

﹢ Shortens your cold,
  works faster™
﹢ Non-drowsy

Nighttime

﹢ Shortens your cold,
  works faster™
﹢ Fall asleep faster,
  naturally
﹢ Non-habit forming

18 MELTS
(Daytime)

QuickMelts®
Natural
Mixed Berry Flavor
Homeopathic

6 MELTS
(Nighttime)